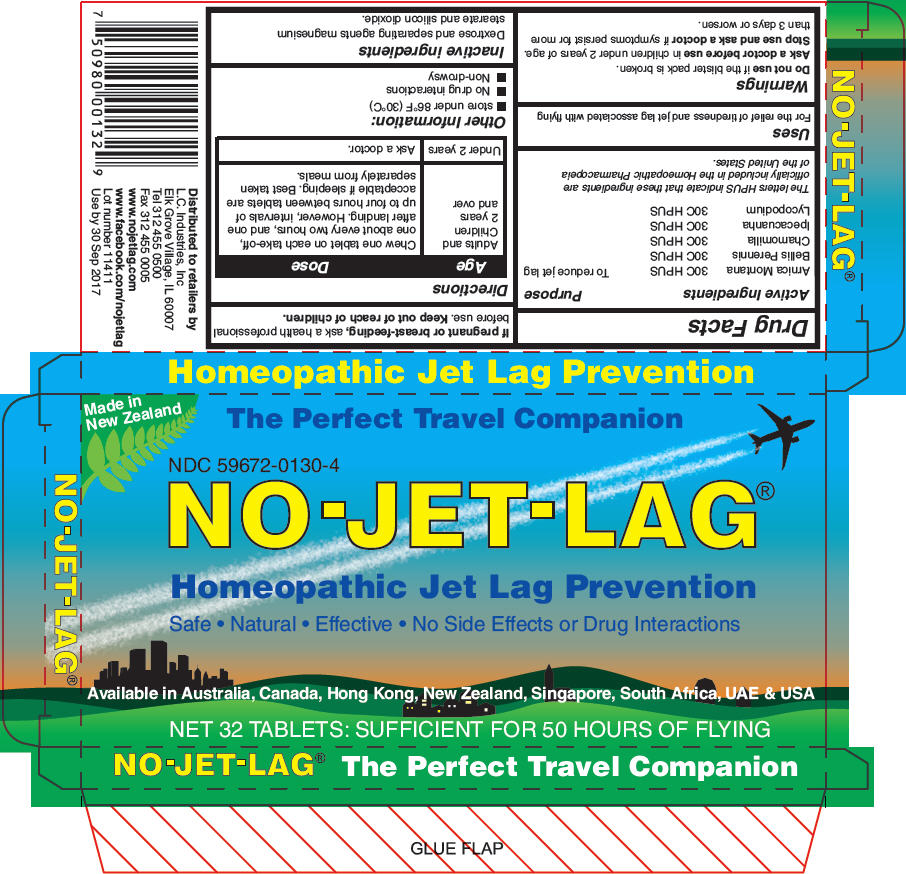 DRUG LABEL: NO-JET-LAG
NDC: 59672-0130 | Form: TABLET
Manufacturer: LC Industries
Category: homeopathic | Type: HUMAN OTC DRUG LABEL
Date: 20140814

ACTIVE INGREDIENTS: Arnica Montana 30 [hp_C]/1 1; Bellis Perennis 30 [hp_C]/1 1; Matricaria Recutita 30 [hp_C]/1 1; Ipecac 30 [hp_C]/1 1; Lycopodium Clavatum Spore 30 [hp_C]/1 1
INACTIVE INGREDIENTS: Dextrose 242 mg/1 1; silicon dioxide; Magnesium stearate

NO-JET-LAG®
Homeopathic Jet Lag Prevention

Drug Facts

ACTIVE INGREDIENT

Active Ingredients |  | Purpose
Arnica Montana | 30C HPUS | To reduce jet lag
Bellis Perennis | 30C HPUS
Chamomilla | 30C HPUS
Ipecacuanha | 30C HPUS
Lycopodium | 30C HPUS

The letters HPUS indicate that these ingredients are officially included in the Homeopathic Pharmacopeia of the United States.

Uses

For the relief of tiredness and jet lag associated with flying

Warnings

Do not use if the blister pack is broken.

Ask a doctor before use in children under 2 years of age.

Stop use and ask a doctor if symptoms persist for more than 3 days or worsen.

PREGNANCY OR BREAST FEEDING

If pregnant or breast-feeding, ask a health professional before use.

Keep out of reach of children.

Directions

Age | Dose
Adults and Children 2 years and over | Chew one tablet on each take-off, one about every two hours, and one after landing. However, intervals of up to four hours between tablets are acceptable if sleeping. Best taken separately from meals.
Under 2 years | Ask a doctor.

Other Information

- store under 86°F (30°C)
- No drug interactions
- Non-drowsy

Inactive ingredients

Dextrose and separating agents magnesium stearate and silicon dioxide.

Distributed to retailers by
L.C. Industries, Inc
Elk Grove Village, IL 60007

PRINCIPAL DISPLAY PANEL - 32 Tablet Carton

Made in
New Zealand

The Perfect Travel Companion

NDC 59672-0130-4
NO-JET-LAG®

Homeopathic Jet Lag Prevention

Safe • Natural • Effective • No Side Effects or Drug Interactions

Available in Australia, Canada, Hong Kong, New Zealand, Singapore, South Africa, UAE & USA

NET 32 TABLETS: SUFFICIENT FOR 50 HOURS OF FLYING